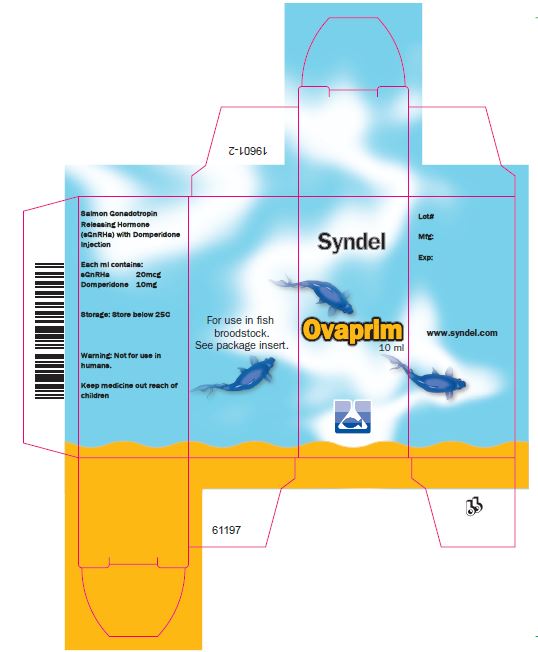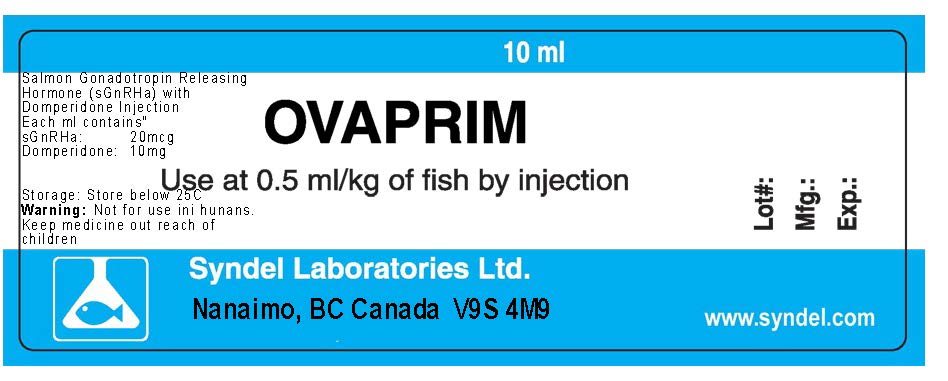 DRUG LABEL: Ovaprim
NDC: 50378-022 | Form: INJECTION, SOLUTION
Manufacturer: Western Chemical Inc.
Category: animal | Type: OTC ANIMAL DRUG LABEL
Date: 20240628

ACTIVE INGREDIENTS: SALMON GONADOTROPIN RELEASING HORMONE D-ARG6 ANALOG ETHYL AMIDE ACETATE 20 ug/1 mL; DOMPERIDONE 10 mg/1 mL

Ovaprim® Injectable Solution
(Salmon Gonadotropin Releasing Hormone Analog 20 µg/ml + Domperidone 10 mg/ml)For intraperitoneal or intramuscular injection

OVAPRIM Injectable Solution

(Salmon Gonadotropin Releasing Hormone Analog 20 µg/ml + Domperidone 10 mg/ml)

For intraperitoneal or intramuscular injection in ornamental finfish broodstock only.

This product is not to be used in animals intended for use as food for humans or food-producing animals.
Not for use in fish whose offspring may be consumed by humans or food-producing animals.
As used on this label, the words “ornamental fish” refer to a wide variety of finfish species maintained primarily for their appearance and do not include any fish that are consumed by humans or food-producing animals.

PRECAUTIONS

CAUTION:
FOR USE IN ORNAMENTAL FINFISH BROODSTOCK ONLY; THIS PRODUCT IS NOT TO BE USED IN
ANIMALS INTENDED FOR USE AS FOOD FOR HUMANS OR OTHER ANIMALS.

WARNING:
Care should be taken to avoid accidental contact or self-injection. In the event of accidental self-injection, seek medical advice immediately. Use in a well ventilated area. Wear gloves, goggles and suitable protective clothing. Not for use in humans. Keep out of the reach of children.

INHALATION: May be harmful. If breathing becomes difficult, move to fresh air, and contact a physician.

INGESTION: May be harmful. If the person is conscious, wash out mouth with copious amounts of water. Contact a physician.

EYE CONTACT: May be harmful. In case of contact, flush with copious amounts of water for at least 15 minutes. Assure adequate flushing by separating eyelids with fingers. Contact a physician.

SKIN CONTACT: May be harmful. In case of contact, flush with copious amounts of water for at least 15 minutes. Remove contaminated clothing and wash before re-using. Contact a physician.

OTHER HEALTH INFORMATION: The toxicological properties of sGnRHa have not been thoroughly investigated. The actions are similar to luteinizing hormone releasing hormone (LHRH, Gonadotropin releasing hormone, GnRH) in humans. LHRH is the key mediator in the liberation of the pituitary gonadotropins, luteinizing hormone (LH) and follicle stimulating hormone (FSH). LHRH may modify reproductive ability by influencing plasma gonadotropin levels and concomitantly gonadal steroid levels.
To obtain a product Safety Data Sheet, call Syndel at sales@syndel.com

DOSAGE AND ADMINISTRATION

DIRECTIONS FOR USE:
Ovaprim® is packaged ready for use in liquid form. Precise amounts for individual injections should be withdrawn directly from the bottle into a syringe. Due to the viscosity of the product, use of syringes with Luer Lock tips or permanently attached needles is strongly recommended. Use of syringes with slip tips is not recommended since needles could inadvertently eject under pressure.

CLEANLINESS: Syringes/needles should be sterile prior to use.

LOADING: Withdraw only enough solution from the bottle of Ovaprim® Injectable Solution as will be required for the weight of the fish. With the needle pointed upward and directed away from your face, squeeze the syringe gently to expel any trapped air.

INJECTION: Hold the fish firmly and insert the needle into the abdominal cavity/belly between the pelvic fin and the vent or into the muscle on either side of the dorsal fin. For intra-abdominal injection in smaller species, it may be helpful to secure the fish on a soft wet surface such as a sponge, and to place the fish on its side and inject into the rear abdominal cavity to avoid contact with internal organs. Inject Ovaprim® carefully. After injection, gently place the fish into a container of clean aerated water.

SEDATION FOR HANDLING AND RECOVERY: If necessary, sedate broodstock prior to Ovaprim® injection.

DOSE:
A general dose of Ovaprim® is 0.5 ml per kilogram of bodyweight. This dose may vary among finfish species and physiological state of individual animals. Environment and temperature also play a significant role in the reproductive process and may affect dose and timing. For most species, only a single dose of Ovaprim® is required; but treatment of fish with a single dose of Ovaprim® is only effective in fish that are within or near their natural spawning season. For other species, a split dose may be needed. For split dosing, a loading dose of 10% of the total dose should be injected, followed by injection of the remaining 90% of the total dose at least 6 hours later. In warm water species, ovulation may occur in as little as 4 hours post treatment, so fish should be monitored accordingly. Signs of ovulation/spermiation may include a noticeable swelling and “softening” of the abdomen; presence of eggs in the water; the ability to easily express eggs from the female and milt from males; and when sexes are held together in the same tank, onset of spawning behavior (e.g., males “chasing” females). However, it is important to note that the interval between treatment and the onset of ovulation is variable between species and temperature, and treated fish should be disturbed as little as possible to reduce stress during final maturation. Males may respond in shorter periods of time than females of the same species.

DOSE CALCULATION:
The dose is calculated based on the weight of the fish.

FISH WEIGHT x OVAPRIM® DOSAGE = AMOUNT OF INJECTION
Examples: 1) 0.2 kg 0.5 ml/kg 0.1 ml
2) 50 gm 0.5 µl/gm 25 µl
Use of a needle guard to limit the penetration of the needle into the fish may be helpful, and use of a tuberculin or similar syringe is also recommended for accurate dosing in small fish and to minimize trauma at the injection site. Intramuscular injection may result in bleeding at the injection site. Swelling, ulceration, whiteness, redness, or hypopigmentation may also be observed at the injection site.

STORAGE AND HANDLING:
Store below 25°C and protect from sunlight and sources of heat.

DISPOSAL:
Contact your State Environmental Control Agency, or the Hazardous Waste Representative at the nearest EPA Regional Office for guidance pertaining to disposal of unused product.

QUESTIONS/COMMENTS? For technical assistance, call Syndel at (888) 912-7431

Syndel
1441 W. Smith Road
Ferndale, WA 98248
www.syndel.com

Rev: June 30, 2023

NDC Number: 50378-022-10